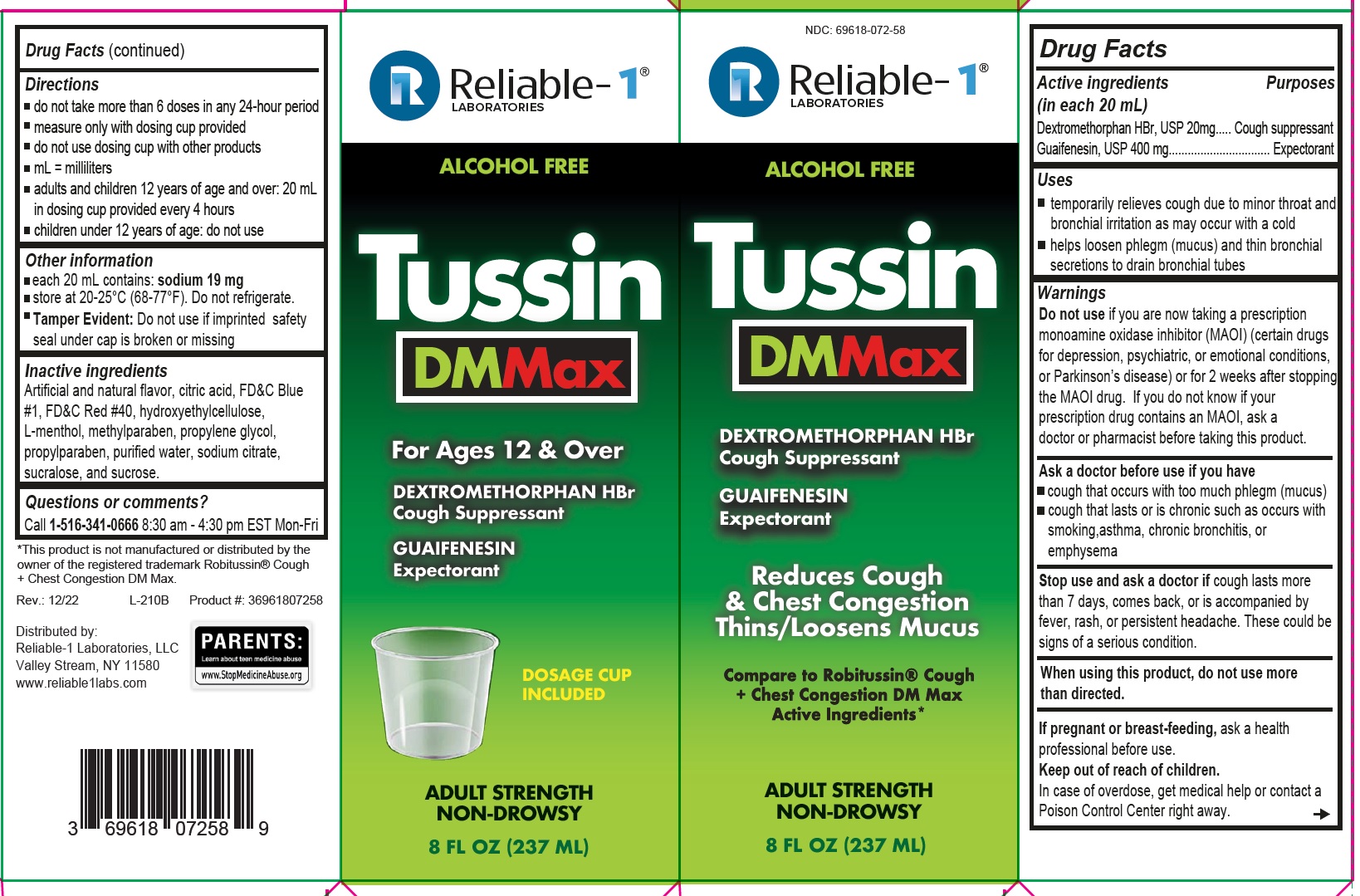 DRUG LABEL: Tussin DMMax
NDC: 69618-072 | Form: LIQUID
Manufacturer: RELIABLE 1 LABORATORIES LLC
Category: otc | Type: HUMAN OTC DRUG LABEL
Date: 20221229

ACTIVE INGREDIENTS: DEXTROMETHORPHAN HYDROBROMIDE 20 mg/20 mL; GUAIFENESIN 400 mg/20 mL
INACTIVE INGREDIENTS: ANHYDROUS CITRIC ACID; FD&C BLUE NO. 1; FD&C RED NO. 40; HYDROXYETHYL CELLULOSE, UNSPECIFIED; MENTHOL; METHYLPARABEN; PROPYLENE GLYCOL; PROPYLPARABEN; WATER; SODIUM CITRATE; SUCRALOSE; SUCROSE

Active Ingredients (in each 20 mL)

Dextromethorphan HBr 20mg

Guaifenesin 400 mg

Purpose

Cough Suppressant

Expectorant

Uses

- temporarily relieves cough due to minor throat and bronchial irritation as may occur with a cold
- helps loosen phlegm (mucus) and thin bronchial secretions to drain bronchial tubes

Warnings

Do not use if you are now taking a prescription monoamine oxidase inhibitor (MAOI) (certain drugs for depression, psychiatric, or emotional conditions, or Parkinson’s disease) or for 2 weeks after stopping the MAOI drug. If you do not know if your prescription drug contains an MAOI, ask a doctor or pharmacist before taking this product.

Ask a doctor before us if you have

- cough that occurs with too much phlegm (mucus)
- cough that lasts or is chronic such as occurs with smoking,asthma, chronic bronchitis, or emphysema

Stop use and ask a doctor if cough lasts more than 7 days, comes back, or is accompanied by fever, rash, or persistent headache. These could be signs of a serious condition.

When using this prodcut, do not use more than directed.

PREGNANCY OR BREAST FEEDING

If pregnant or breast-feeding, ask a health professional before use.

Keep out of reach of children. In case of overdose, get medical help or contact a Poison Control Center right away.

Directions

- do not take more than 6 doses in any 24-hour period
- measure only with dosing cup provided
- do not use dosing cup with other products
- mL = mililiters
- adults and children 12 years of age and over: 20 mL in dosing cup provided every 4 hours
- children under 12 years of age: do not use

Inactive ingredients

Artificial and natural flavor, citric acid, FD&C Blue #1, FD&C Red #40, hydroxyethylcellulose, L-menthol, methylparaben, propylen glycol, propylparaben, purified water, sodium citrate, sucralose, and sucrose.

Questions or comments?

Call 1-516-341-0666 8:30 am - 4:30 pm EST Mon-Fri